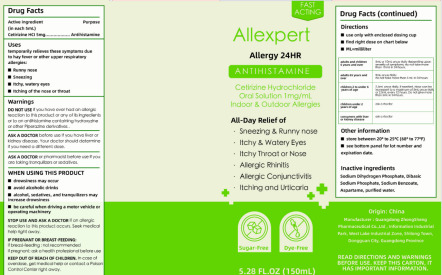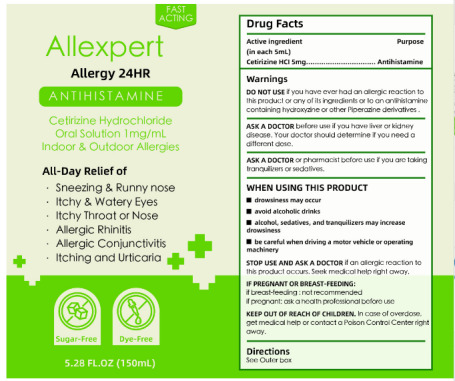 DRUG LABEL: Allexpert 24HR Antihistamine Cetirizine Hydrochloride Oral Solution
NDC: 84264-001 | Form: SOLUTION
Manufacturer: Bowong Technology (ShenZhen) Co.,Ltd
Category: otc | Type: HUMAN OTC DRUG LABEL
Date: 20240417

ACTIVE INGREDIENTS: CETIRIZINE HYDROCHLORIDE 1 mg/1 mL
INACTIVE INGREDIENTS: SODIUM BENZOATE; ASPARTAME; SODIUM PHOSPHATE, DIBASIC; WATER; AZITHROMYCIN SODIUM DIHYDROGEN PHOSPHATE

Active Ingredient(s)

Cetirizine HCI 5mg.(in each 5ml)

Purpose

Antihistamine

Use

temporarily relieves these symptoms due to hay fever or other upper respiratory allergies:
■Runny nose
■Sneezing
■Itchy, watery eyes
■Itching of the nose or throat

Warnings

1.ASK A DOCTOR before use if you have Iver or kidney disoaso. Your doctor should dotermine iI you need a dilferent dose.
2.ASK A DOCTOR or phamaclst belore use i you aro taking tranqulzors or sodativcs.

Do not use

if you have over had an allorgic reaclion lo ths product or any ol ils ingredients or to an anlihislamine conlaining hydroxydine
or other Piperazine derivatives .

WHEN USING

■drowsiness may occur
■avoid alcoholic drinks
■alcohol, sedatives, and tranquilizers may increase drowsiness
■be careful when driving a motor vehicle or operating machinery

STOP USE

if an allergic reoclion lo this product occurs. Seek medical help right away.

KEEP OUT OF REACH OF CHILDREN

In cose of overdose. get medical help or contact a Poison Control Center right away.

Directions

See Outer box

Other information

■store between 20* to 25C (68* to 77*F)

■see bottom panel for lot number and expiration date.

Inactive ingredients

Sodium Dihydrogen Phosphate, Dibasic
Sodium Phosphate, Sodium Benzoate,
Aspartame, purified water.